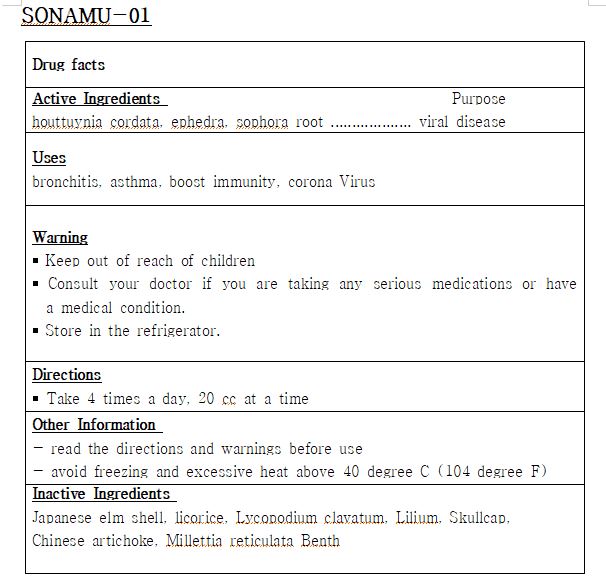 DRUG LABEL: SONAMU-01
NDC: 82664-0001 | Form: LIQUID
Manufacturer: sonamu oriental medical
Category: otc | Type: HUMAN OTC DRUG LABEL
Date: 20220408

ACTIVE INGREDIENTS: HOUTTUYNIA CORDATA WHOLE 3 g/100 mL; SOPHORA FLAVESCENS ROOT 3 g/100 mL
INACTIVE INGREDIENTS: WATER

Drug Facts

ACTIVE INGREDIENT

houttuynia cordata, ephedra, sophora root

PURPOSE

bronchitis, asthma, boost immunity, corona Virus

KEEP OUT OF REACH OF THE CHILDREN

INDICATIONS AND USAGE

Take 4 times a day, 20 cc at a time

￭ Keep out of reach of children

￭ Consult your doctor if you are taking any serious medications or have a medical condition.

￭ Store in the refrigerator.

DOSAGE AND ADMINISTRATION

for oral use only

INACTIVE INGREDIENT

Japanese elm shell, licorice, Lycopodium clavatum, Lilium, Skullcap,

Chinese artichoke, Millettia reticulata Benth